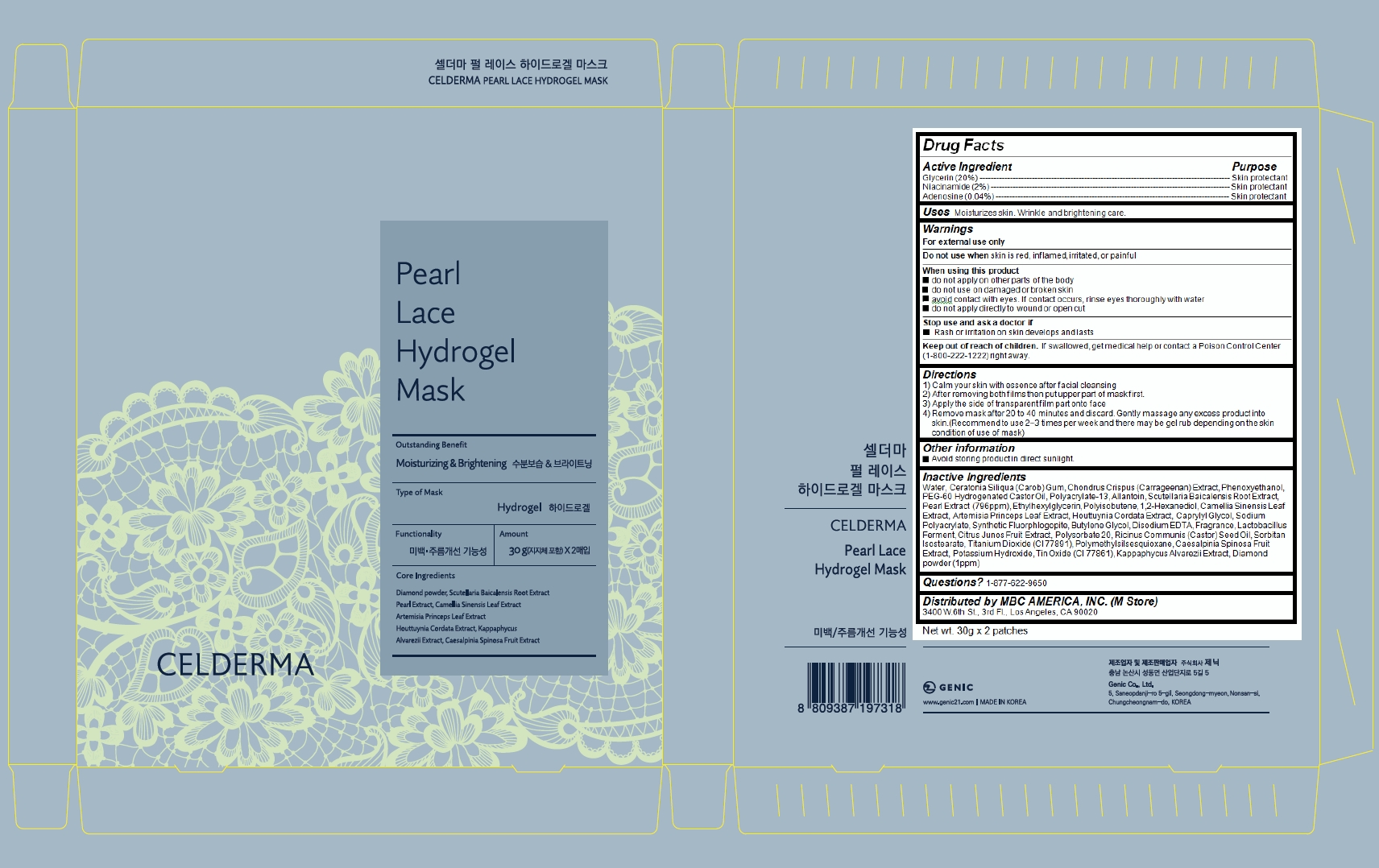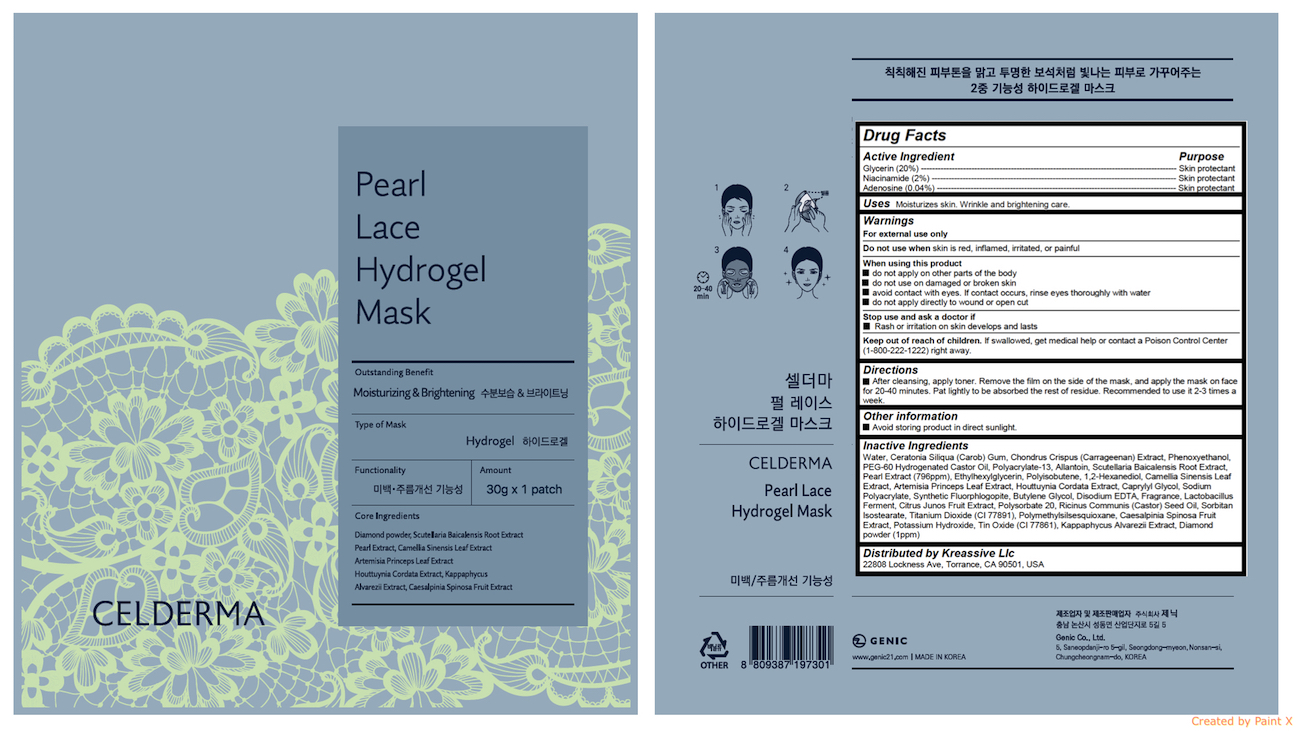 DRUG LABEL: CELDERMA Pearl Lace Hydrogel Mask
NDC: 72044-107 | Form: PATCH
Manufacturer: GENIC CO., LTD
Category: otc | Type: HUMAN OTC DRUG LABEL
Date: 20191231

ACTIVE INGREDIENTS: ADENOSINE 0.012 g/30 g; NIACINAMIDE 0.6 g/30 g; GLYCERIN 6 g/30 g
INACTIVE INGREDIENTS: WATER; CHONDRUS CRISPUS CARRAGEENAN; PHENOXYETHANOL; ALLANTOIN; ETHYLHEXYLGLYCERIN; 1,2-HEXANEDIOL; GREEN TEA LEAF; ARTEMISIA PRINCEPS LEAF; SODIUM POLYACRYLATE (2500000 MW); HOUTTUYNIA CORDATA FLOWERING TOP; SCUTELLARIA BAICALENSIS ROOT; CAPRYLYL GLYCOL; PEG-60 HYDROGENATED CASTOR OIL

CELDERMA Pearl Lace Hydrogel Mask

Active ingredients

Glycerin (20%)

Niacinamide (2%)

Adenosine (0.04%)

Purpose

skin protectatn

Uses

Moisturizes skin. Wrinkle and brightening care.

Warnings

For external use only

Do not use when skin is red, inflamed, irritated, or painful

When using this product

- do not apply on other parts of the body
- do not use on damaged or broken skin
- avoid contact with eyes. If contact occurs, rinse eyes thoroughly with water
- do not apply directly to wound or open cut

Stop use and ask a doctor if

- Rash or irritation on skin develops and lasts

Keep out of reach of children

If swallowed, get medical help or contact a Poison Control Center (1-800-222-1222) right away.

Directions

fter cleansing, apply toner. Remove the film on the side of the mask, and apply the mask on face for 20-40 minutes. Pat lightly to be absorbed the rest of residue. Recommended to use it 2-3 times a week.

Inactive ingredients

Water, Ceratonia Siliqua (Carob) Gum, Chondrus Crispus (Carrageenan) Extract, Phenoxyethanol, PEG-60 Hydrogenated Castor Oil, Polyacrylate-13, Allantoin, Scutellaria Baicalensis Root Extract, Pearl Extract (796ppm), Ethylhexylglycerin, Polyisobutene, 1,2-Hexanediol, Camellia Sinensis Leaf Extract, Artemisia Princeps Leaf Extract, Houttuynia Cordata Extract, Caprylyl Glycol, Sodium Polyacrylate, Synthetic Fluorphlogopite, Butylene Glycol, Disodium EDTA, Fragrance, Lactobacillus Ferment, Citrus Junos Fruit Extract, Polysorbate 20, Ricinus Communis (Castor) Seed Oil, Sorbitan Isostearate, Titanium Dioxide (CI 77891), Polymethylsilsesquioxane, Caesalpinia Spinosa Fruit Extract, Potassium Hydroxide, Tin Oxide (CI 77861), Kappaphycus Alvarezii Extract, Diamond powder (1ppm)